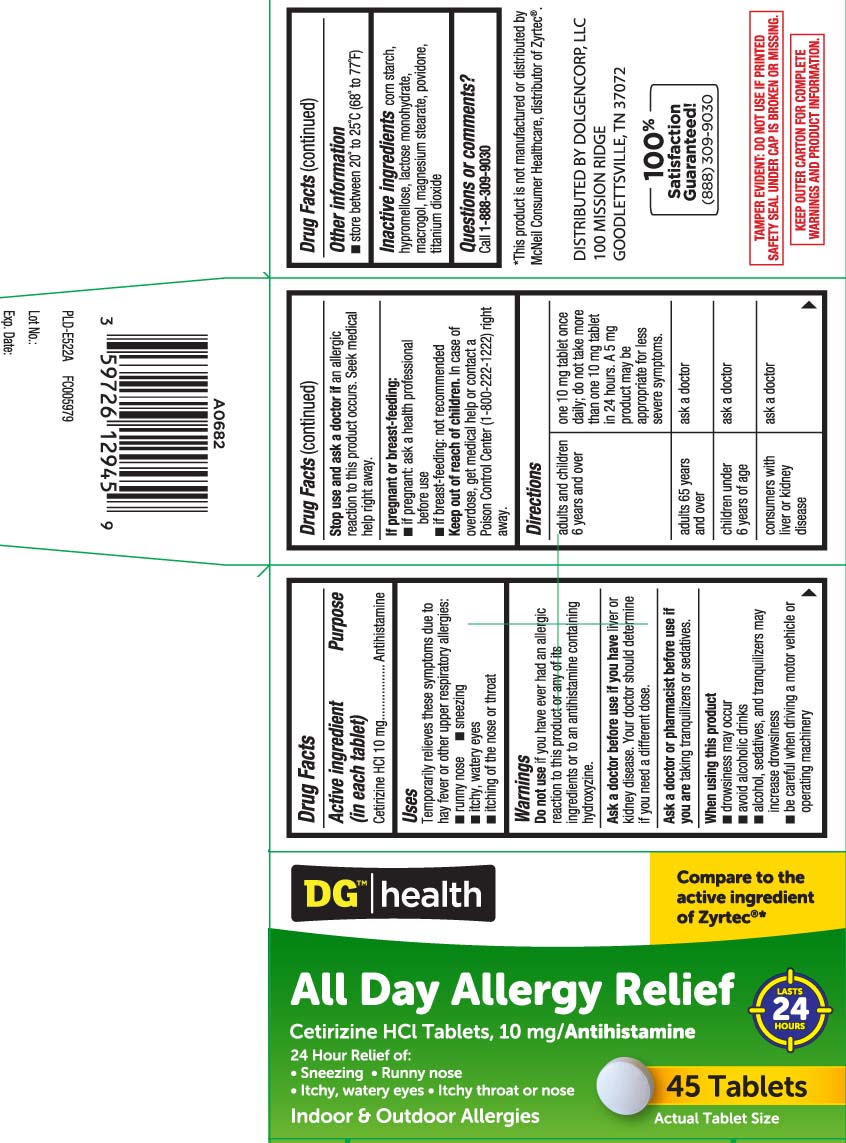 DRUG LABEL: All Day Allergy Relief
NDC: 55910-039 | Form: TABLET
Manufacturer: Dolgencorp, Inc.  (DOLLAR GENERAL & REXALL)
Category: otc | Type: HUMAN OTC DRUG LABEL
Date: 20250701

ACTIVE INGREDIENTS: CETIRIZINE HYDROCHLORIDE 10 mg/1 1
INACTIVE INGREDIENTS: STARCH, CORN; HYPROMELLOSE, UNSPECIFIED; LACTOSE MONOHYDRATE; MAGNESIUM STEARATE; CELLULOSE, MICROCRYSTALLINE; POVIDONE; TITANIUM DIOXIDE; POLYETHYLENE GLYCOL, UNSPECIFIED

Cetirizine Hydrochloride Tablets

Active Ingredient (in each tablet)

Cetirizine HCl 10 mg

Purpose

Antihistamine

Uses

temporarily relieves these symptoms due to hay fever or other upper respiratory allergies:

- runny nose
- sneezing
- itchy, watery eyes
- itching of the nose or throat

Do not use

if you have ever had an allergic reaction to this product or any of its ingredients or to an antihistamine containing hydroxyzine.

Ask a doctor before use if you have

liver or kidney disease. Your doctor should determine if you need a different dose.

Ask a doctor or pharmacist before use if you are

taking tranquilizers or sedatives.

When using this product

- drowsiness may occur
- alcohol, sedatives, and tranquilizers may increase drowsiness
- avoid alcoholic drinks
- be careful when driving a motor vehicle or operating machinery

Stop use and ask a doctor if

an allergic reaction to this product occurs. Seek medical help right away.

If pregnant or breast-feeding

- if breast-feeding: not recommended
- if pregnant: ask a health professional before use.

Keep out of reach of children

In case of overdose, get medical help or contact a Poison Control Center (1-800-222-1222) right away.

Directions

Adults and children 6 years and over | One 10 mg tablet once daily; do not take more than one 10 mg tablet in 24 hours. A 5 mg product may be appropriate for less severe symptoms.
Adults 65 years and over | ask a doctor.
Children under 6 years of age | ask a doctor
Consumers with liver or kidney disease | ask a doctor

Other Information

- store between 20º to 25o C (68o to 77o F)

Inactive ingredients

corn starch, hypromellose, lactose monohydrate, macrogol, magnesium stearate, povidone, titanium dioxide

Questions or comments?

Call 1-888-309-9030

Principal Display Panel

Compare to the active ingredient in Zyrtec®*

All Day Allergy Relief

Cetirizine HCL Tablets, 10 mg/Antihistamine

24-hour Relief of:

- Sneezing
- Runny Nose
- Itchy, Watery Eyes
- Itchy Throat or Nose

Indoor & Outdoor Allergies

Tablets

*This product is not manufactured or distributed by McNeil Consumer Healthcare, distributor of Zyrtec®

TAMPER EVIDENT: DO NOT USE IF PRINTED SAFETY SEAL UNDER CAP IS BROKEN OR MISSING

KEEP OUTER CARTON FOR COMPLETE WARNINGS AND PRODUCT INFORMATION.

DISTRIBUTED BY DOLGENCORP, LLC

100 MISSION RIDGE

GOODLETTSVILLE, TN 37072

Product Label

DOLLAR GENERAL HEALTH All Day Allergy Relief